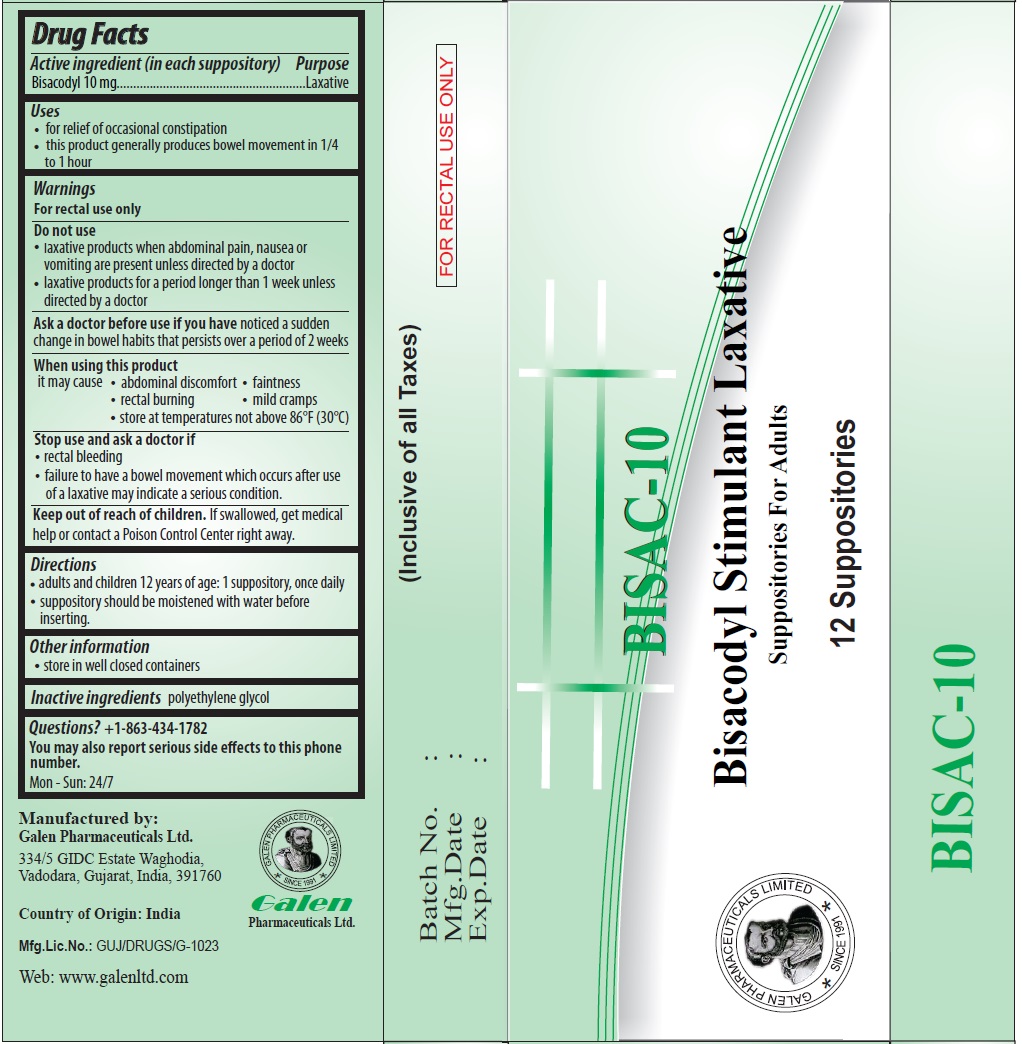 DRUG LABEL: BISAC-10 Bisacodyl Stimulant Laxative
NDC: 81440-102 | Form: SUPPOSITORY
Manufacturer: GALEN PHARMACEUTICALS LIMITED
Category: otc | Type: HUMAN OTC DRUG LABEL
Date: 20230428

ACTIVE INGREDIENTS: BISACODYL 10 mg/1 1
INACTIVE INGREDIENTS: POLYETHYLENE GLYCOL, UNSPECIFIED

BISAC-10

Active ingredient (in each suppository)

Bisacodyl 10 mg

Purpose

Laxative

Uses

• for relief of occasional constipation
• this product generally produces bowel movement in 1/4 to 1 hour

Warnings

For rectal use only

Do not use
• laxative products when abdominal pain, nausea or vomiting are present unless directed by a doctor
• laxative products for a period longer than 1 week unless directed by a doctor

Ask a doctor before use if you have noticed a sudden change in bowel habits that persists over a period of 2 weeks

When using this product
it may cause • abdominal discomfort • faintness
• rectal burning • mild cramps
• store at temperatures not above 86°F (30°C)

Stop use and ask a doctor if
• rectal bleeding
• failure to have a bowel movement which occurs after use of a laxative may indicate a serious condition.

Keep out of reach of children. If swallowed, get medical help or contact a Poison Control Center right away.

Directions

• adults and children 12 years of age: 1 suppository, once daily
• suppository should be moistened with water before inserting.

Other information

• store in well closed containers

Inactive ingredients

polyethylene glycol

Questions? +1-863-434-1782

You may also report serious side effects to this phone number.
Mon - Sun: 24/7

Bisacodyl Stimulant Laxative

Suppositories For Adults

FOR RECTAL USE ONLY

Manufactured by:
Galen Pharmaceuticals Ltd.
334/5 GIDC Estate Waghodia,
Vadodara, Gujarat, India, 391760

Country of Origin: India

Web: www.galenltd.com